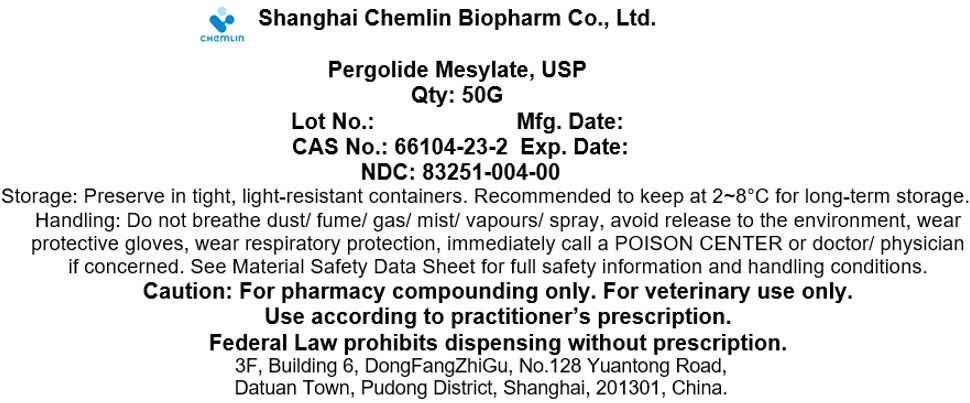 DRUG LABEL: Pergolide Mesylate
NDC: 83251-004 | Form: POWDER
Manufacturer: Shanghai Chemlin Biopharm Co., Ltd.
Category: other | Type: BULK INGREDIENT - ANIMAL DRUG
Date: 20241003

ACTIVE INGREDIENTS: Pergolide Mesylate 1 g/1 g

Pergolide Mesylate